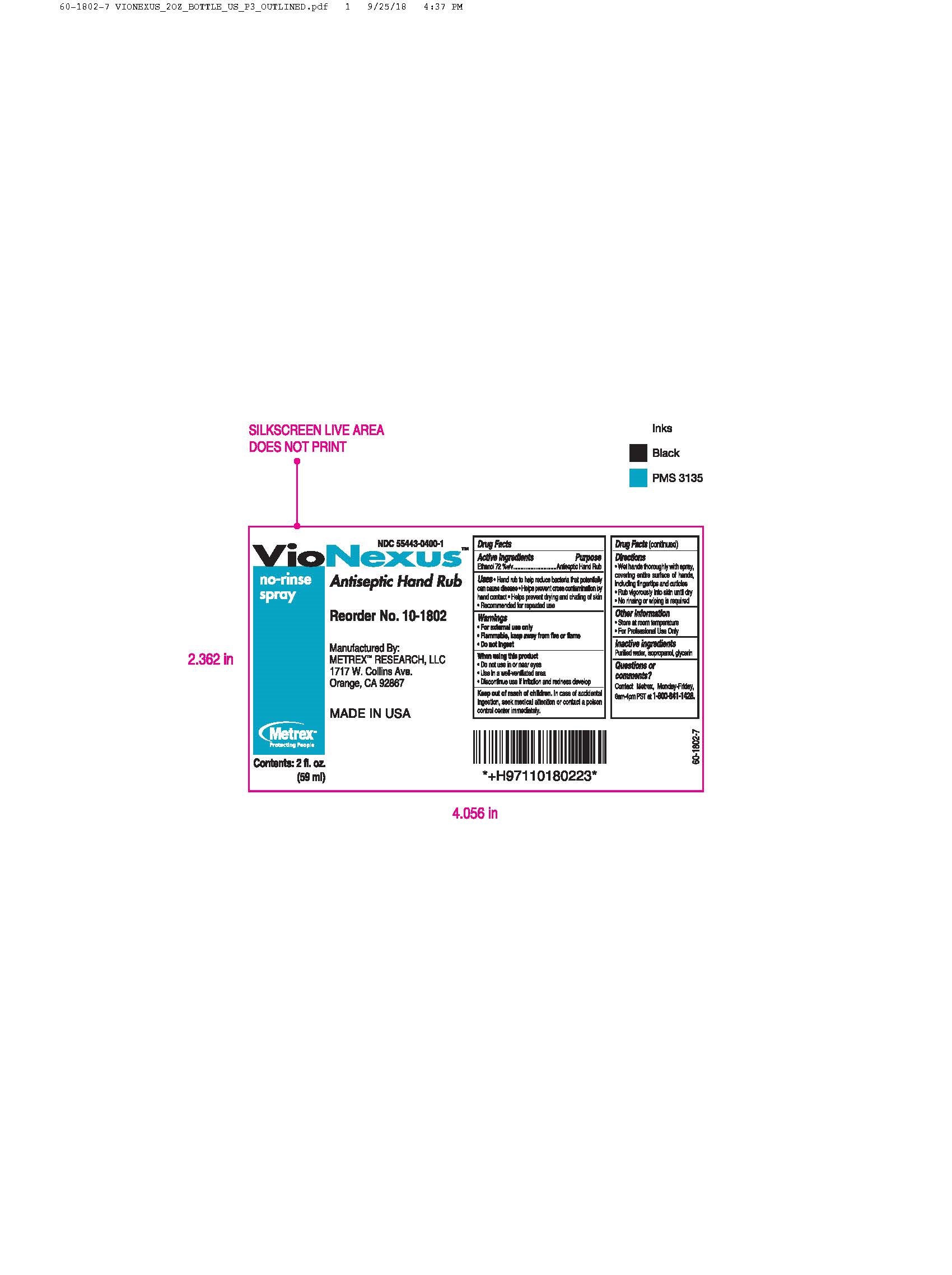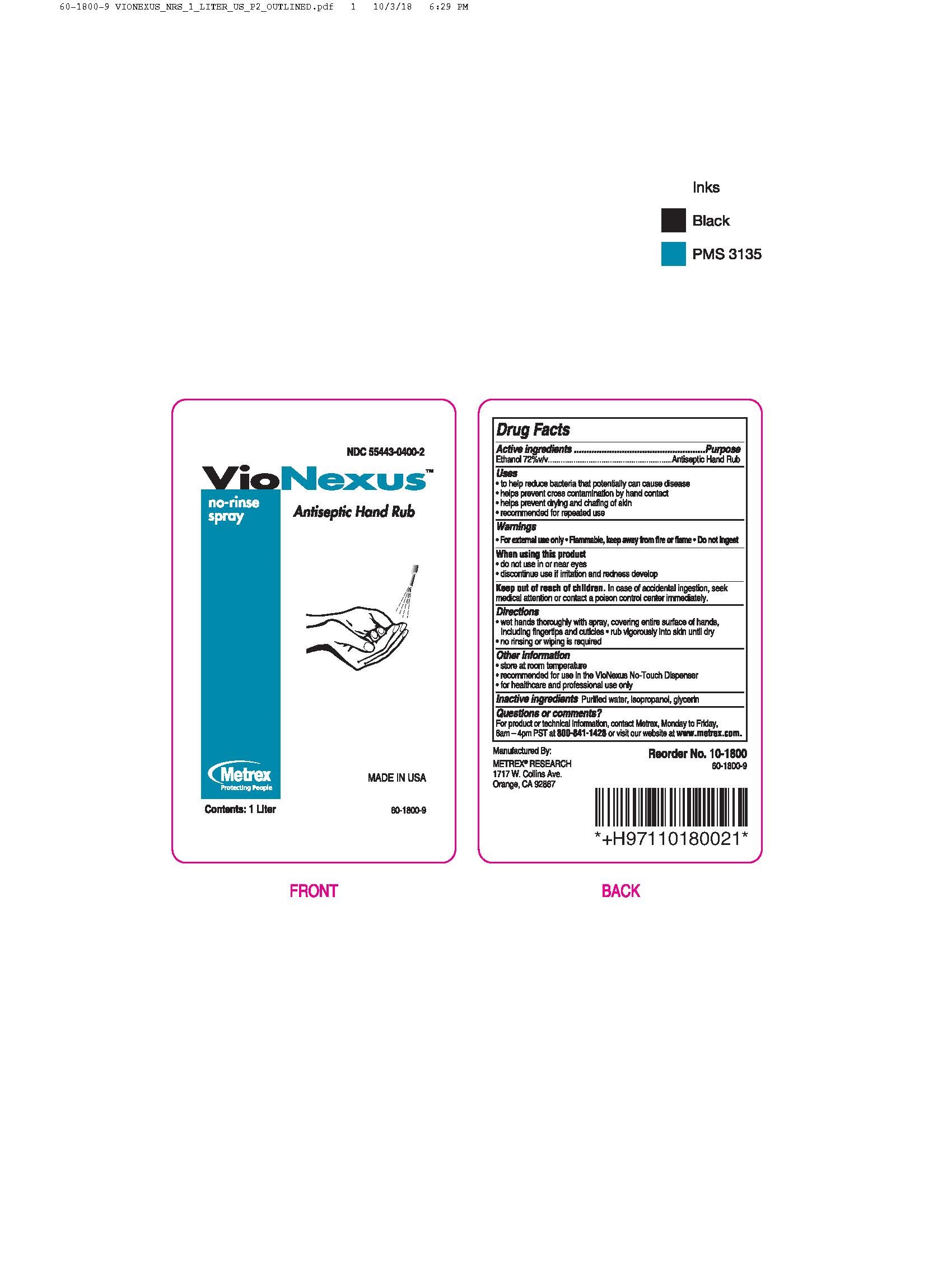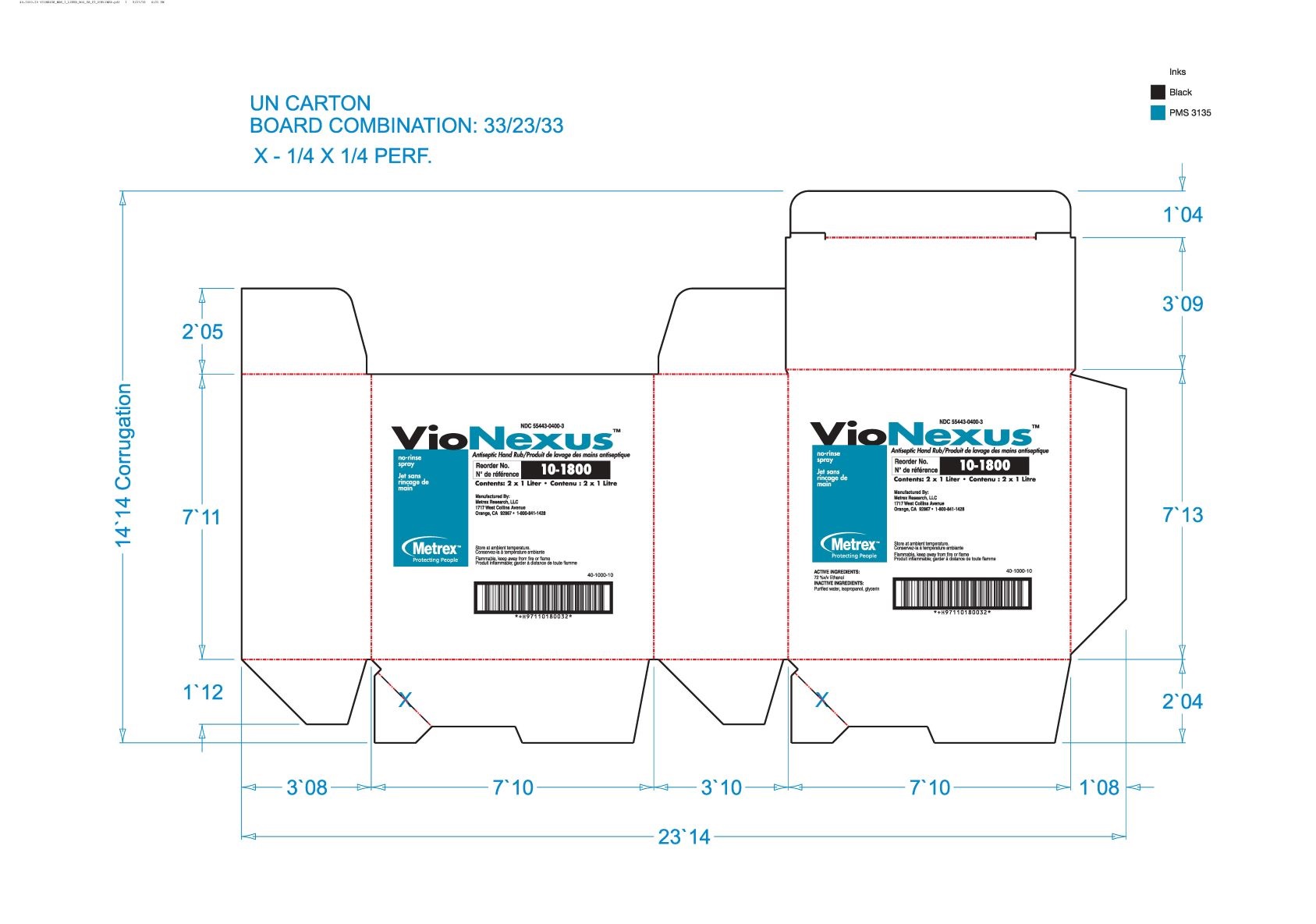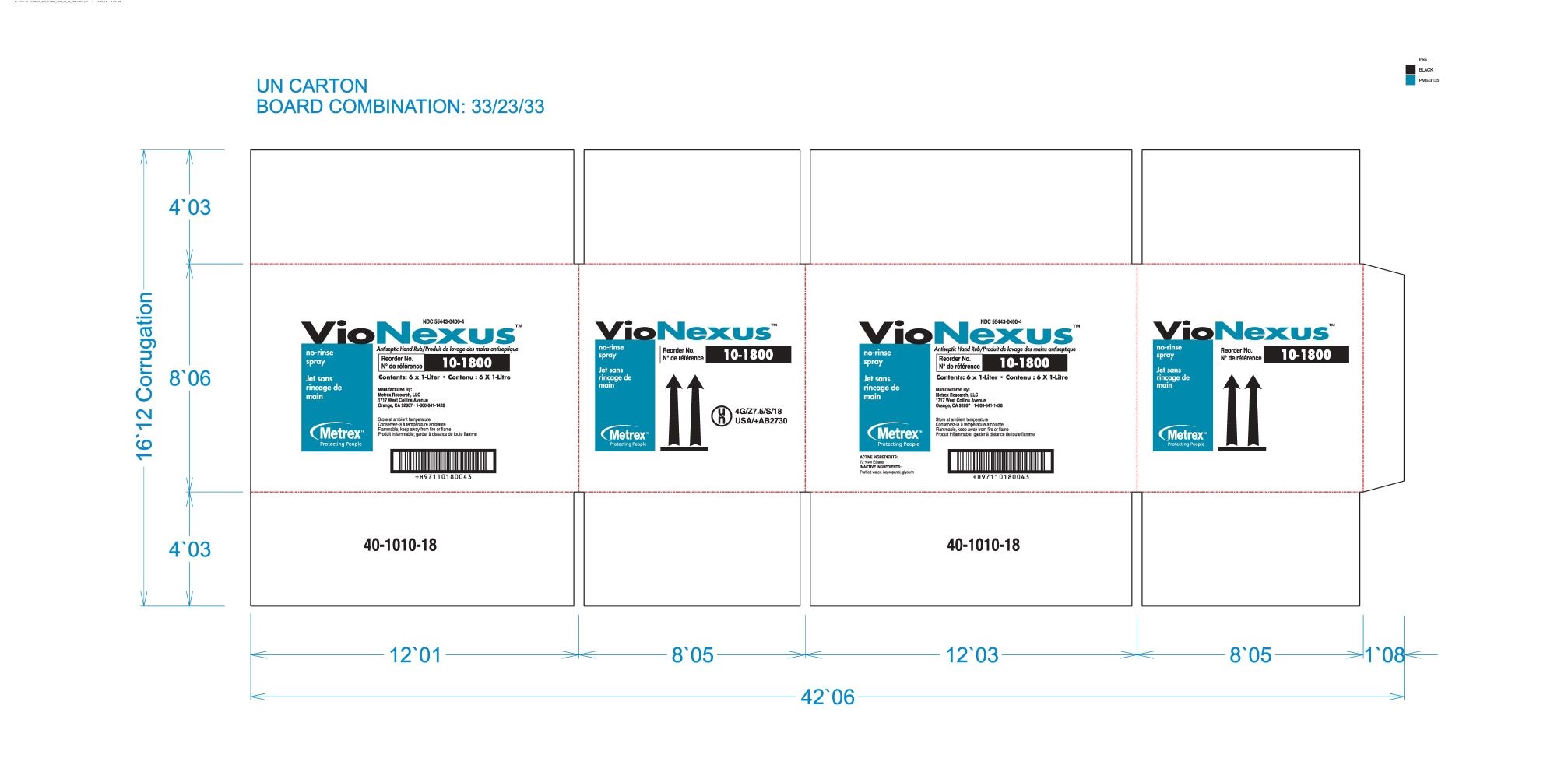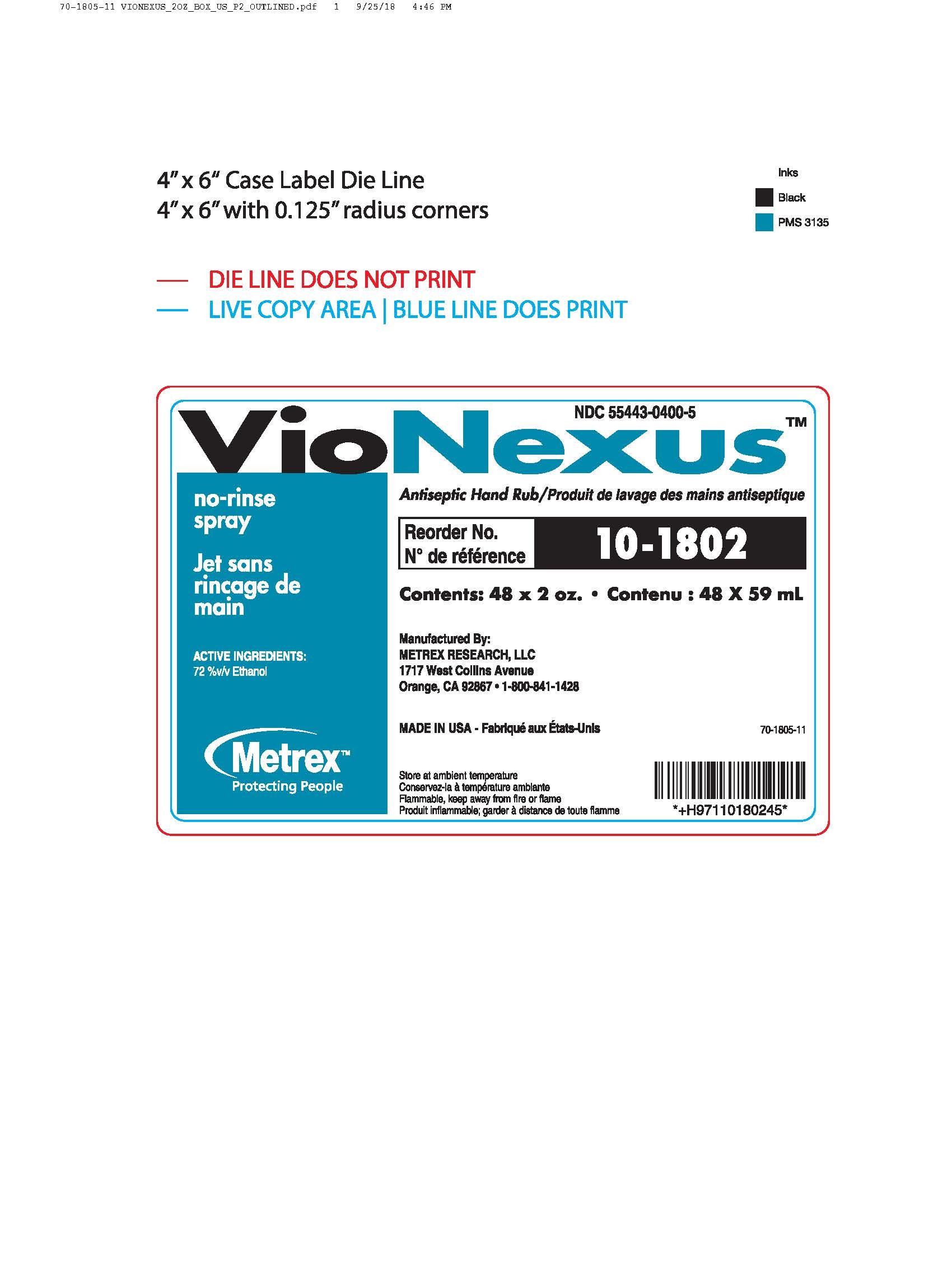 DRUG LABEL: VIONEXUS
NDC: 55443-0400 | Form: LIQUID
Manufacturer: METREX RESEARCH, LLC
Category: otc | Type: HUMAN OTC DRUG LABEL
Date: 20241007

ACTIVE INGREDIENTS: ALCOHOL 72 mL/100 mL
INACTIVE INGREDIENTS: WATER; GLYCERIN; ISOPROPYL ALCOHOL

VioNexus No Rinse Spray

Warnings

- For external use only
- Flammable, keep away from fire or flame
- Do not ingest

When using this product

- do not use in or near eyes
- discontinue use if irritation and redness develop

Keep out of reach of children

In case of accidental ingestion, seek medical attention or contact a poison control center immediately.

Uses

- to help reduce bacteria that potentially can case disease
- helps prevent cross contamination by hand contact
- helps prevent drying and chafing of skin
- recommended for repeated use

Active ingredients

Ethanol 72%v/v

Purpose

Antiseptic Hand Rub

Directions

- wet hands thoroughly with spray, covering entire surface of hands, including finger tips and cuticles
- rub vigorously into skin until dry
- no rinsing or wiping is required

Other information

- store at room temperature
- recommended for us in the Vionexus No-Touch Dispenser
- for healthcare and professional use only

Inactive ingredients

Purified water, isopropanol, glycerin

Questions or comments?

For product or technical information, contact Metrex, Monday to Friday, 6am - 4pm PST at 800-841-1428 or visit our website at www.metrex.com.

Dosage and Administration Route(s)

- Administration Route(s): Topical - Administration to a particular spot on the outer surface of the body.
- Dosage Form: Liquid - A dosage form consisting of a pure chemical in its liquid state.